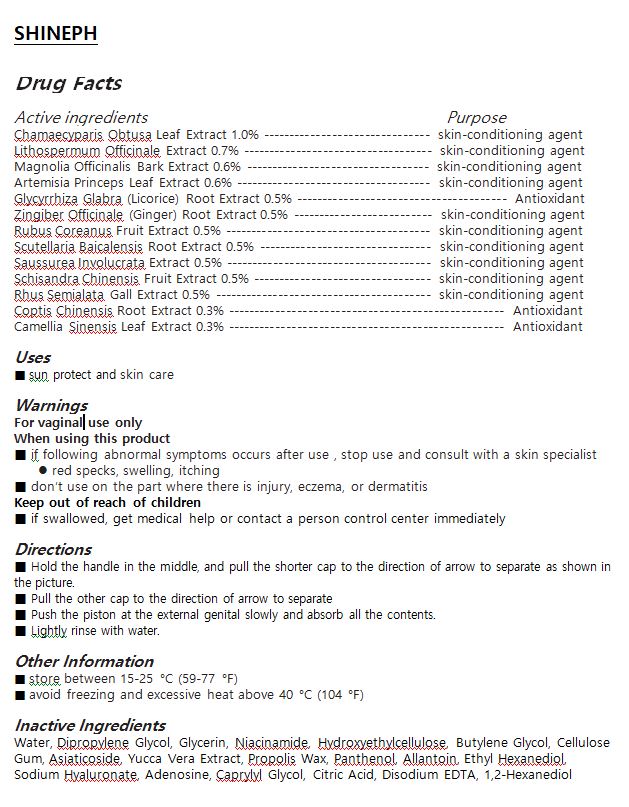 DRUG LABEL: SHINEPH
NDC: 73305-0001 | Form: LIQUID
Manufacturer: CH Bio Co., Ltd.
Category: otc | Type: HUMAN OTC DRUG LABEL
Date: 20190906

ACTIVE INGREDIENTS: LITHOSPERMUM OFFICINALE ROOT 0.7 g/100 g; ARTEMISIA PRINCEPS LEAF OIL 0.6 g/100 g; MAGNOLIA OFFICINALIS BARK 0.6 g/100 g; CHAMAECYPARIS OBTUSA LEAF 1 g/100 g
INACTIVE INGREDIENTS: WATER

Drug Facts

ACTIVE INGREDIENT

Chamaecyparis Obtusa Leaf extract, Lithospermum Officinale Extract, Magnolia Officinalis Bark Extract , Artemisia Princeps Leaf Extract , Glycyrrhiza Glabra (Licorice) Root Extract , Zingiber Officinale (Ginger) Root Extract , Rubus Coreanus Fruit Extract , Scutellaria Baicalensis Root Extract , Saussurea Involucrata Extract , Schisandra Chinensis Fruit Extract , Rhus Semialata Gall Extract , Coptis Chinensis Root Extract , Camellia Sinensis Leaf Extract

INACTIVE INGREDIENT

Water, Dipropylene Glycol, Glycerin, Niacinamide, Hydroxyethylcellulose, Butylene Glycol, Cellulose Gum, Asiaticoside, Yucca Vera Extract, Propolis Wax, Panthenol, Allantoin, Ethyl Hexanediol, Sodium Hyaluronate, Adenosine, Caprylyl Glycol, Citric Acid, Disodium EDTA, 1,2-Hexanediol

PURPOSE

helps to clean the vulva and smell of women

keep out of reach of the children

INDICATIONS AND USAGE

Hold the handle in the middle, and pull the shorter cap to the direction of arrow to separate as shown in the picture.

Pull the other cap to the direction of arrow to separate

Push the piston at the external genital slowly and absorb all the contents.

Lightly rinse with water.

WARNINGS

1 In the use of the product if the following phenomenon happen, please stop using; if continue using the situation gets worse, please consult with the doctor
1) red, itchy, tingling
2) please stop using if any of the above symptoms appear because of the sun exposure
2 Wounds, eczema, skin inflammation in the face, please do not use
3 Storage precautions
1) seale immediately after using
2) please place in theplace where the infant are unable to access in case eating by mistake
3) avoid placing in high temperature, low temperature or direct sunlight field

DOSAGE AND ADMINISTRATION

for vaginal use only